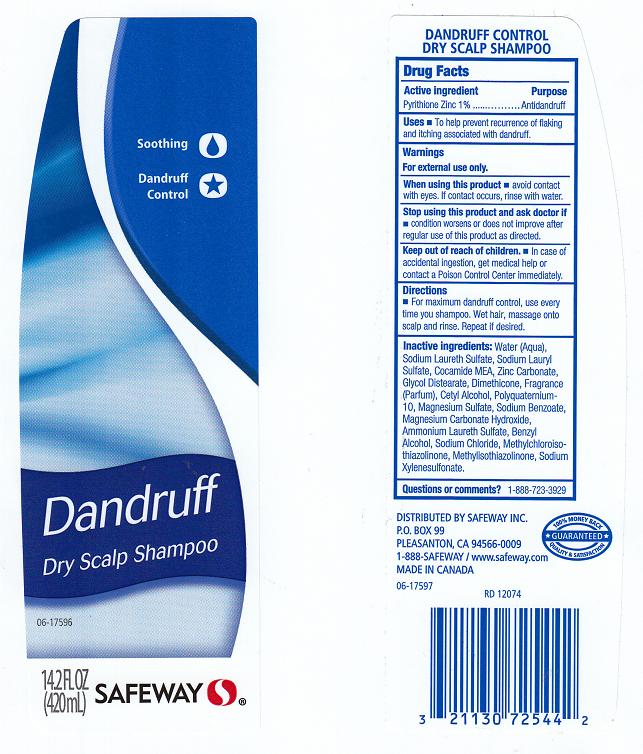 DRUG LABEL: SAFEWAY
NDC: 21130-416 | Form: SHAMPOO
Manufacturer: SAFEWAY INC.
Category: otc | Type: HUMAN OTC DRUG LABEL
Date: 20120529

ACTIVE INGREDIENTS: PYRITHIONE ZINC 1.0 mL/100 mL
INACTIVE INGREDIENTS: WATER; SODIUM LAURETH SULFATE; SODIUM LAURYL SULFATE; COCO MONOETHANOLAMIDE; ZINC CARBONATE; GLYCOL DISTEARATE; DIMETHICONE; CETYL ALCOHOL; POLYQUATERNIUM-10 (400 CPS AT 2%); MAGNESIUM SULFATE; SODIUM BENZOATE; MAGNESIUM CARBONATE HYDROXIDE; AMMONIUM LAURETH-3 SULFATE; BENZYL ALCOHOL; SODIUM CHLORIDE; METHYLCHLOROISOTHIAZOLINONE; METHYLISOTHIAZOLINONE; SODIUM XYLENESULFONATE

DRUG FACTS

ACTIVE INGREDIENT

PYRITHIONE ZINC 1%

PURPOSE

ANTIDANDRUFF

USES

TO HELP PREVENT RECURRENCE OF FLAKING AND ITCHING ASSOCIATED WITH DANDRUFF.

WARNINGS

FOR EXTERNAL USE ONLY.

WHEN USING THIS PRODUCT

AVOID CONTACT WITH EYES. IF CONTACT OCCURS, RINSE WITH WATER.

STOP USING THIS PRODUCT AND ASK DOCTOR IF

CONDITION WORSENS OR DOES NOT IMPROVE AFTER REGULAR USE OF THIS PRODUCT AS DIRECTED.

KEEP OUT OF REACH OF CHILDREN

IN CASE OF ACCIDENTAL INGESTION, GET MEDICAL HELP OR CONTACT A POISON CONTROL CENTER IMMEDIATELY.

DIRECTIONS

FOR MAXIMUM DANDRUFF CONTROL, USE EVERY TIME YOU SHAMPOO. WET HAIR, MASSAGE ONTO SCALP AND RINSE. REPEAT IF DESIRED.

INACTIVE INGREDIENTS:

WATER (AQUA), SODIUM LAURETH SULFATE, SODIUM LAURYL SULFATE, COCAMIDE MEA, ZINC CARBONATE, GLYCOL DISTEARATE, DIMETHICONE, FRAGRANCE (PARFUM), CETYL ALCOHOL, POLYQUATERNIUM-10, MAGNESIUM SULFATE, SODIUM BENZOATE, MAGNESIUM CARBONATE HYDROXIDE, AMMONIUM LAURETH SULFATE, BENZYL ALCOHOL, SODIUM CHLORIDE, METHYLCHLOROISOTHIAZOLINONE, METHYLISOTHIAZOLINONE, SODIUM XYLENESULFONATE.

QUESTIONS OR COMMENTS?

1-888-723-3929